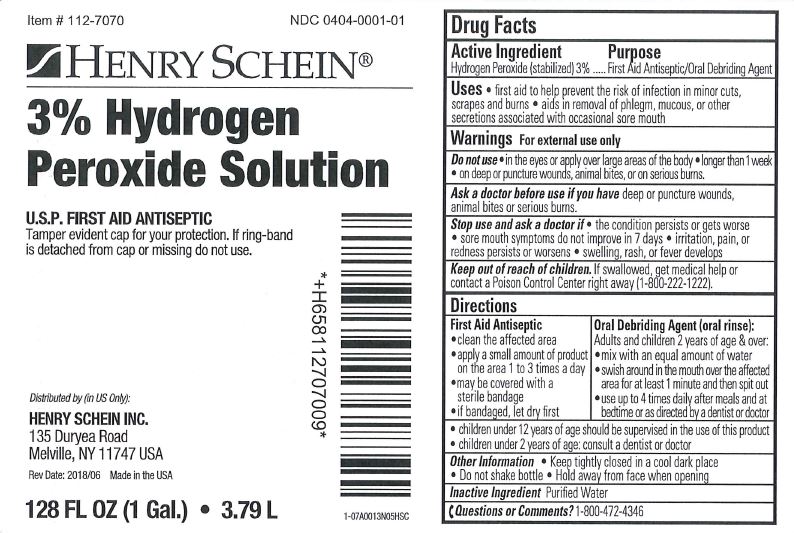 DRUG LABEL: Hydrogen Peroxide
NDC: 0404-0001 | Form: SOLUTION
Manufacturer: Henry Schein Inc.
Category: otc | Type: HUMAN OTC DRUG LABEL
Date: 20241115

ACTIVE INGREDIENTS: HYDROGEN PEROXIDE 30 mg/1 mL
INACTIVE INGREDIENTS: WATER

Hydrogen Peroxide

Drug Facts

Active Ingredient

Hydrogen Peroxide (stabilized) 3%

Purpose

First Aid Antiseptic/Oral Debriding Agent

Uses

- first aid to help prevent the risk of infection in minor cuts, scrapes and burns
- aids in removal of phlegm, mucous, or other secretions associated with occasional sore mouth

Warnings

For external use only

Do not use

- in the eyes or apply over large areas of the body
- longer than 1 week

Ask a doctor before use if you havedeep puncture wounds, animal bites or serious burns.

Stop use and ask a doctor if

- the condition persists or gets worse
- sore mouth symptoms do not improve in 7 days
- irritation, pain, or redness persists or worsens
- swelling, rash, or fever develops

Keep out of reach of children.If swallowed, get medical help or contact a Poison Control Center right away (1-800-222-1222).

Directions

First Aid Antiseptic

- clean the affected area
- apply a small amount of product on the area 1 to 3 times a day
- may be covered with a sterile bandage
- if bandaged, let dry first

Oral Debriding Agent (oral rinse):

Adults and children 2 years of age & over:

- mix with an equal amount of water
- swish around in the mouth over the affected area for at least 1 minute and then spit out
- use up to 4 times daily after meals and at bedtime or as directed by a dentist or doctor

- children under 12 years of age should be supervised in the use of this product
- children under 2 years of age: consult a dentist or doctor

Other Information

- Keep tightly closed in a cool dark place
- Do not shake bottle
- Hold away from face when opening

Inactive Ingredient

Purified Water

Questions or Comments?

1-800-472-4346

PRINCIPAL DISPLAY PANEL - 3.79 L Bottle Label

Item # 112-7070
NDC 0404-0001-01

HENRY SCHEIN®

3 % Hydrogen
Peroxide Solution

U.S.P. FIRST AID ANTISEPTIC
Tamper evident cap for your protection. If ring-band
is detached from cap or missing do not use.

Distributed by (in US Only):

HENRY SCHEIN INC.
135 Duryea Road
Melville, NY 11747 USA

Rev. Date 2018/06 Made in the USA

128 FL OZ (1 Gal.) • 3.79 L